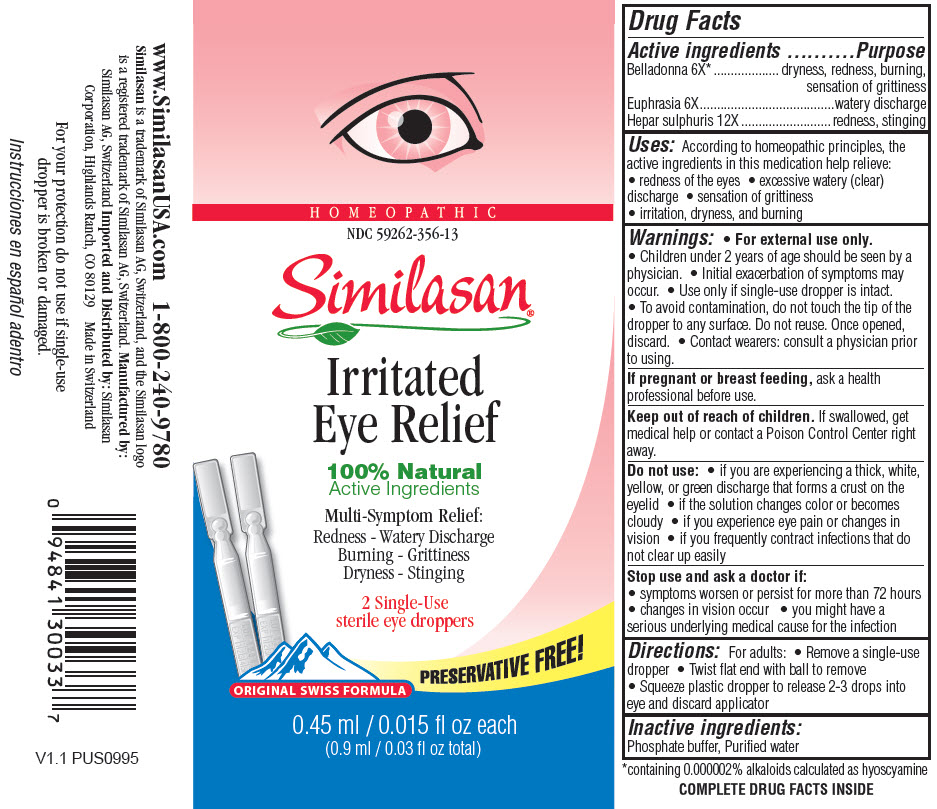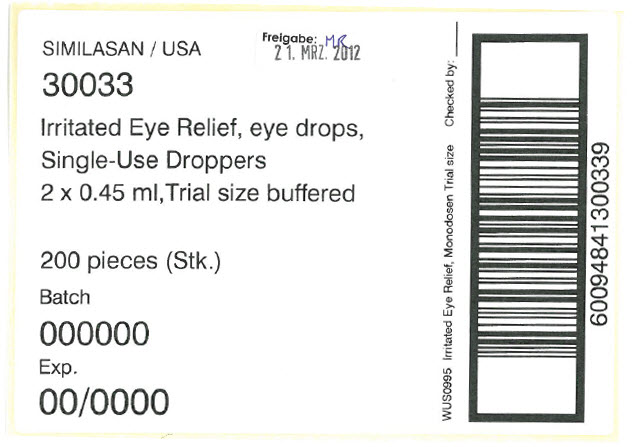 DRUG LABEL: Irritated Eye Relief
NDC: 59262-356 | Form: SOLUTION/ DROPS
Manufacturer: Similasan Corporation
Category: homeopathic | Type: HUMAN OTC DRUG LABEL
Date: 20190320

ACTIVE INGREDIENTS: ATROPA BELLADONNA 6 [hp_X]/0.45 mL; EUPHRASIA STRICTA 6 [hp_X]/0.45 mL; CALCIUM SULFIDE 12 [hp_X]/0.45 mL
INACTIVE INGREDIENTS: WATER

Similasan Irritated Eye Relief

Active Ingredient

Belladonna 6X*
*containing 0.000002% alkaloids calculated as hyoscyamine

Purpose

dryness, redness, burning, sensation of grittiness

Active Ingredient

Euphrasia 6X

Purpose

watery discharge

Active Ingredient

Hepar sulphuris 12X

Purpose

redness, stinging

Uses:

According to homeopathic principles, the active ingredients in this medication help relieve:

- redness of the eyes
- excessive watery (clear) discharge
- sensation of grittiness
- irritation, dryness, and burning

Warnings:

- For external use only.
- Children under 2 years of age should be seen by a physician.
- Initial exacerbation of symptoms may occur.
- Use only if single-use dropper is intact.
- To avoid contamination, do not touch the tip of the dropper to any surface. Do not reuse. Once opened, discard.
- Contact wearers: consult a physician prior to using.

If pregnant or breast feeding,

ask a health professional before use.

Keep out of reach of children.

If swallowed, get medical help or contact a Poison Control Center right away.

Do Not Use:

- if you are experiencing a think, white, yellow, or green discharge that forms a crust on the eyelid
- if the solution changes color or becomes cloudy
- if you experience eye pain or changes in vision
- if you frequently contract infections that do not clear up easily

Stop use and ask a doctor if:

- symptoms worsen or persist for more than 72 hours
- changes in vision occur
- you might have a serious underlying medical cause for the infection

Directions:

For adults:

- Remove a single-use dropper
- Twist flat end with ball to remove
- Squeeze plastic dropper to release 2-3 drops into eye and discard applicator

Inactive ingredients:

Phosphate buffer, Purified water

Prinicipal Display Panel

HOMEOPATHIC
NDC 59262-356-13
Similasan
Irritated
Eye Relief
sterile eye droppers
0.45 ml / 0.015 fl oz each
(0.9 ml / 0.03 fl oz total)

Prinicipal Display Panel

SIMILASAN / USA
30033
Irritated Eye Relief, eye drops,
Single-Use Droppers
2 x 0.45 ml, Trial size buffered
200 pieces (Stk.)
Batch
000000
Exp.
00/0000